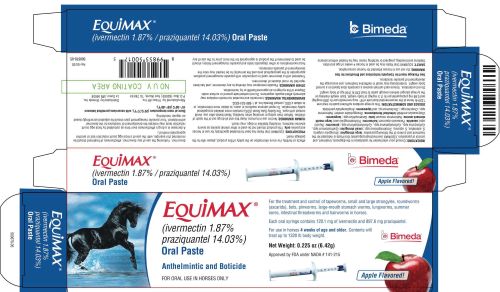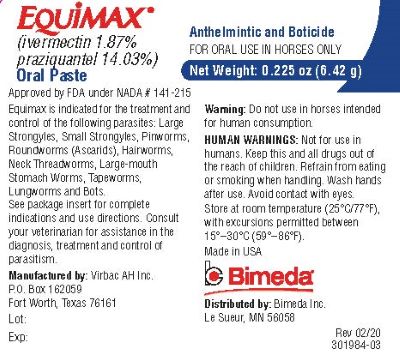 DRUG LABEL: Equimax
NDC: 61133-7000 | Form: PASTE
Manufacturer: Bimeda, Inc.
Category: animal | Type: OTC ANIMAL DRUG LABEL
Date: 20200821

ACTIVE INGREDIENTS: ivermectin 200 ug/1 1; praziquantel 1.5 mg/1 1

Equimax®
(ivermectin 1.87% / praziquantel 14.03%)
Oral Paste
Anthelmintic and Boticide

GENERAL PRECAUTIONS

FOR ORAL USE IN HORSES ONLY

For the treatment and control of worms and bots in horses with a single dose.

Safe for horses 4 weeks of age and older. Contents will treat up to 1320 lb body weight.

Net Weight: 0.225 oz (6.42 g)

INDICATIONS

Consult your veterinarian for assistance in the diagnosis, treatment and control of parasitism.
EQUIMAX (ivermectin/praziquantel) Oral Paste is indicated for the treatment and control of the following parasites:
Tapeworms
Anoplocephala perfoliata
Large Strongyles (adults)
Strongylus vulgaris (also early forms in blood vessels)
S. edentatus (also tissue stages)
S. equinus
Triodontophorus spp.
Small Strongyles (adults, including those resistant to some benzimidazole class compounds)
Cyathostomum spp.
Cylicocyclus spp.
Cylicostephanus spp.
Cylicodontophorus spp.
Small Strongyles (fourth-stage larvae)
Pinworms (adults and fourth-stage larvae)
Oxyuris equi
Ascarids (adults and third- and fourth-stage larvae)
Parascaris equorum
Hairworms (adults)
Trichostrongylus axei
Large-mouth Stomach Worms (adults)
Habronema muscae
Bots (oral and gastric stages)
Gasterophilus spp.
Lungworms (adults and fourth-stage larvae)
Dictyocaulus arnfieldi
Intestinal Threadworms (adults)
Strongyloides westeri
Summer Sores caused by Habronema and Draschia spp. cutaneous third-stage larvae
Dermatitis caused by Neck Threadworm microfilariae, Onchocerca sp.

DOSAGE AND ADMINISTRATION

This syringe contains sufficient paste to treat one 1320-lb horse at the recommended dose rate of 91 mcg ivermectin per lb (200 mcg/kg) and 0.68 mg praziquantel per lb (1.5 mg/kg) of body weight. Each weight marking on the syringe plunger delivers enough paste to treat 220 lb (100 kg) of body weight.

1. While holding plunger, turn the knurled ring on the plunger 1/4 turn to the left and slide it so the side nearest the barrel is at the prescribed weight marking.
2. Lock the ring in place by making a 1/4 turn to the right.
3. Make sure that the horse’s mouth contains no feed.
4. Remove the cover from the tip of the syringe.
5. Insert the syringe tip into the horse’s mouth at the space between the teeth.
6. Depress the plunger as far as it will go, depositing paste on the back of the tongue.
7. Immediately raise the horse’s head for a few seconds after dosing.
Do not underdose. Ensure each animal receives a complete dose based on a current body weight. Underdosing may result in ineffective treatment, and encourage the development of parasite resistance.

Parasite Control Program: All horses should be included in a regular parasite control program with particular attention being paid to
mares, foals, and yearlings. Foals should be treated initially at 4 weeks of age, and routine treatment repeated as appropriate. Consult
your veterinarian for a control program to meet your specific needs. EQUIMAX Oral Paste effectively controls gastrointestinal
nematodes, cestodes and bots of horses. Regular treatment will reduce the chances of colic caused by Anoplocephala perfoliata and
verminous arteritis caused by Strongylus vulgaris.

Product Advantages: Broad-spectrum Control: EQUIMAX Oral Paste kills important internal parasites, including tapeworms, bots and
the arterial stages of S. vulgaris, with a single dose. EQUIMAX Oral Paste contains two potent antiparasitic agents that are neither
benzimidazoles nor organophosphates.

SAFETY

EQUIMAX Oral Paste may be used in horses 4 weeks of age and older. Stallions and breeding, pregnant or lactating mares
may be treated without adverse effects on fertility.

In a tolerance study in which 3- to 4-week-old foals were treated at 10X once, loose watery stools were observed on
post-treatment days 1, 2, and 5-9 in one foal. These signs resolved without treatment by day 10, and no other foals were affected.

In a reproductive safety study, eleven mares were treated with a 3X dose of EQUIMAX Oral Paste every two weeks throughout
breeding, pregnancy and lactation, up until the foal was three months of age. Ten mares served as controls and were treated with the
vehicle paste in a similar manner. An increased incidence of colic was observed in treated mares as compared to control mares. In
addition, elevations of GGT and AST were more frequent in the 3X treated mares, and in two mares these enzymes were elevated at the
time of colic episodes.

One treated mare was dropped from the study because she did not conceive after three breeding attempts.

Two treated mares had abnormally short diestrous periods of two days and eight days on the first estrous cycle following the birth of
the study foal. In addition, one of these two mares failed to ovulate in the second and third estrous cycles.

In the first few weeks of life, foals born to the 3X treated mares had a higher incidence of transient ocular discharge and gastrointestinal
disturbances (loose stools, diarrhea) and depression requiring medical intervention as compared to foals born to control mares.

PRECAUTIONS

EQUIMAX Oral Paste has been formulated specifically for use in horses and ponies only. This product should not be used in other animal species as severe adverse reactions, including fatalities in dogs, may result.

WARNING

Do not use in horses intended for human consumption.

HUMAN WARNINGS

Not for use in humans. Keep this and all drugs out of the reach of children. Refrain from eating or smoking when handling. Wash hands after use. Avoid contact with eyes. The Safety Data Sheet (SDS) contains more detailed occupational safety information. To report adverse reactions in users, to obtain more information, or to obtain a SDS, contact Bimeda Inc. at 1-888-524-6332.

ENVIRONMENTAL WARNINGS

Ivermectin and excreted ivermectin residues may adversely affect aquatic organisms. Do not contaminate ground or surface water. Dispose of the syringe in an approved landfill or by incineration.

POST APPROVAL EXPERIENCE

(Rev. 2010): The following adverse events are based on post-approval adverse drug experience reporting with Equimax. Not all adverse reactions are reported to FDA CVM. It is not always possible to reliably estimate the adverse event frequency or establish a causal relationship to product exposure using these data.

The following adverse events are listed in decreasing order of reporting frequency: Abdominal pain, diarrhea, depression/lethargy
and anorexia.

To report side effects, call Bimeda Inc. at 1-888-524-6332. For additional information about reporting side effects for animal drugs,
contact FDA at 1-888-FDA-VETS or www.fda.gov/reportanimalae.

OTHER WARNINGS

Parasite resistance may develop to any dewormer, and has been reported for most classes of dewormers.

Treatment with a dewormer used in conjunction with parasite management practices appropriate to the geographical area and the animal(s) to be treated may slow the development of parasite resistance.

Fecal examinations or other diagnostic tests and parasite management history should be used to determine if the product is appropriate for the herd, prior to the use of any dewormer. Following the use of any dewormer, effectiveness of treatment should be monitored (for example, with the use of a fecal egg count reduction test or another appropriate method).

A decrease in a drug's effectiveness over time as calculated by fecal egg count reduction tests may indicate the development of resistance to the dewormer administered. Your parasite management plan should be adjusted accordingly based on regular monitoring.

STORAGE

Store at room temperature (25°C/77°F), with excursions permitted between 15°–30°C (59°–86°F).

NOTE TO USER

Swelling and itching reactions after treatment with ivermectin paste have occurred in horses carrying heavy infections of neck threadworm (Onchocerca sp. microfilariae). These reactions were most likely the result of microfilariae dying in large numbers. Symptomatic treatment may be advisable. Consult your veterinarian should any such reactions occur. Healing of summer sores involving extensive tissue changes may require other appropriate therapy in conjunction with treatment with EQUIMAX Oral Paste. Reinfection, and measures for its prevention, should also be considered. Consult your veterinarian if the condition does not improve.

To report adverse reactions, call Bimeda Inc. at 1-888-524-6332.

Approved by FDA under NADA # 141-215

Manufactured by:
Virbac AH Inc.
P.O. Box 162059
Fort Worth, TX 76161

Made in USA

Equimax is a Registered Trademark of Virbac SA.
301985-03
Rev 02/20

Distributed by:
Bimeda, Inc.
Le Sueur, MN 56058